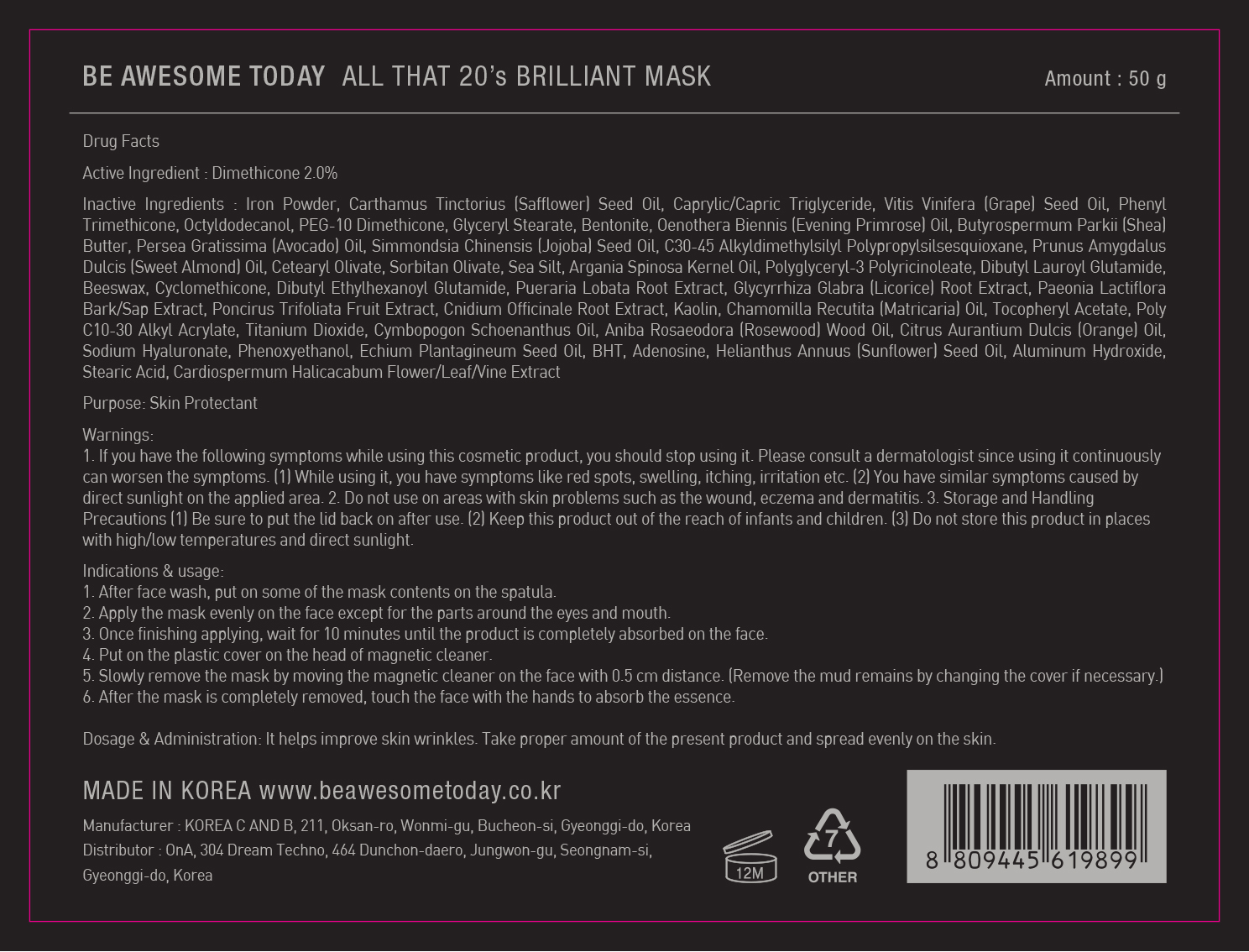 DRUG LABEL: Be Awesome Today All That 20s Brilliant Mask
NDC: 71060-010 | Form: CREAM
Manufacturer: ONA
Category: otc | Type: HUMAN OTC DRUG LABEL
Date: 20190124

ACTIVE INGREDIENTS: DIMETHICONE 1 g/50 g
INACTIVE INGREDIENTS: PHENYL TRIMETHICONE; OCTYLDODECANOL

ACTIVE INGREDIENT

Active Ingredient: Dimethicone 2.0%

INACTIVE INGREDIENT

Inactive Ingredients: Iron Powder, Carthamus Tinctorius (Safflower) Seed Oil, Caprylic/Capric Triglyceride, Vitis Vinifera (Grape) Seed Oil, Phenyl Trimethicone, Octyldodecanol, PEG-10 Dimethicone, Glyceryl Stearate, Bentonite, Oenothera Biennis (Evening Primrose) Oil, Butyrospermum Parkii (Shea) Butter, Persea Gratissima (Avocado) Oil, Simmondsia Chinensis (Jojoba) Seed Oil, C30-45 Alkyldimethylsilyl Polypropylsilsesquioxane, Prunus Amygdalus Dulcis (Sweet Almond) Oil, Cetearyl Olivate, Sorbitan Olivate, Sea Silt, Argania Spinosa Kernel Oil, Polyglyceryl-3 Polyricinoleate, Dibutyl Lauroyl Glutamide, Beeswax, Cyclomethicone, Dibutyl Ethylhexanoyl Glutamide, Pueraria Lobata Root Extract, Glycyrrhiza Glabra (Licorice) Root Extract, Paeonia Lactiflora Bark/Sap Extract, Poncirus Trifoliata Fruit Extract, Cnidium Officinale Root Extract, Kaolin, Chamomilla Recutita (Matricaria) Oil, Tocopheryl Acetate, Poly C10-30 Alkyl Acrylate, Titanium Dioxide, Cymbopogon Schoenanthus Oil, Aniba Rosaeodora (Rosewood) Wood Oil, Citrus Aurantium Dulcis (Orange) Oil, Sodium Hyaluronate, Phenoxyethanol, Echium Plantagineum Seed Oil, BHT, Adenosine, Helianthus Annuus (Sunflower) Seed Oil, Aluminum Hydroxide, Stearic Acid, Cardiospermum Halicacabum Flower/Leaf/Vine Extract

PURPOSE

Purpose: Skin Protectant

WARNINGS

Warnings: 1. If you have the following symptoms while using this cosmetic product, you should stop using it. Please consult a dermatologist since using it continuously can worsen the symptoms. (1) While using it, you have symptoms like red spots, swelling, itching, irritation etc. (2) You have similar symptoms caused by direct sunlight on the applied area. 2. Do not use on areas with skin problems such as the wound, eczema and dermatitis. 3. Storage and Handling Precautions (1) Be sure to put the lid back on after use. (2) Keep this product out of the reach of infants and children. (3) Do not store this product in places with high/low temperatures and direct sunlight.

KEEP OUT OF REACH OF CHILDREN

Keep this product out of the reach of infants and children.

INDICATIONS & USAGE

Indications & usage: 1. After face wash, put on some of the mask contents on the spatula. 2. Apply the mask evenly on the face except for the parts around the eyes and mouth. 3. Once finishing applying, wait for 10 minutes until the product is completely absorbed on the face. 4. Put on the plastic cover on the head of magnetic cleaner. 5. Slowly remove the mask by moving the magnetic cleaner on the face with 0.5 cm distance. (Remove the mud remains by changing the cover if necessary.) 6. After the mask is completely removed, touch the face with the hands to absorb the essence.

DOSAGE & ADMINISTRATION

Dosage & Administration: It helps improve skin wrinkles. Take proper amount of the present product and spread evenly on the skin.